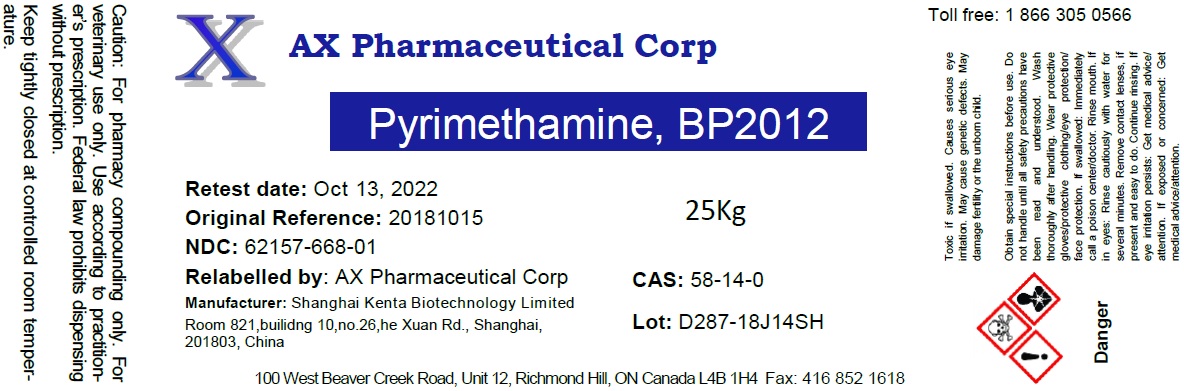 DRUG LABEL: Pyrimethamine
NDC: 62157-705 | Form: POWDER
Manufacturer: AX Pharmaceutical Corp
Category: other | Type: BULK INGREDIENT
Date: 20181030

ACTIVE INGREDIENTS: PYRIMETHAMINE 24.75 kg/25 kg
INACTIVE INGREDIENTS: WATER

Pyrimethamine BP2012